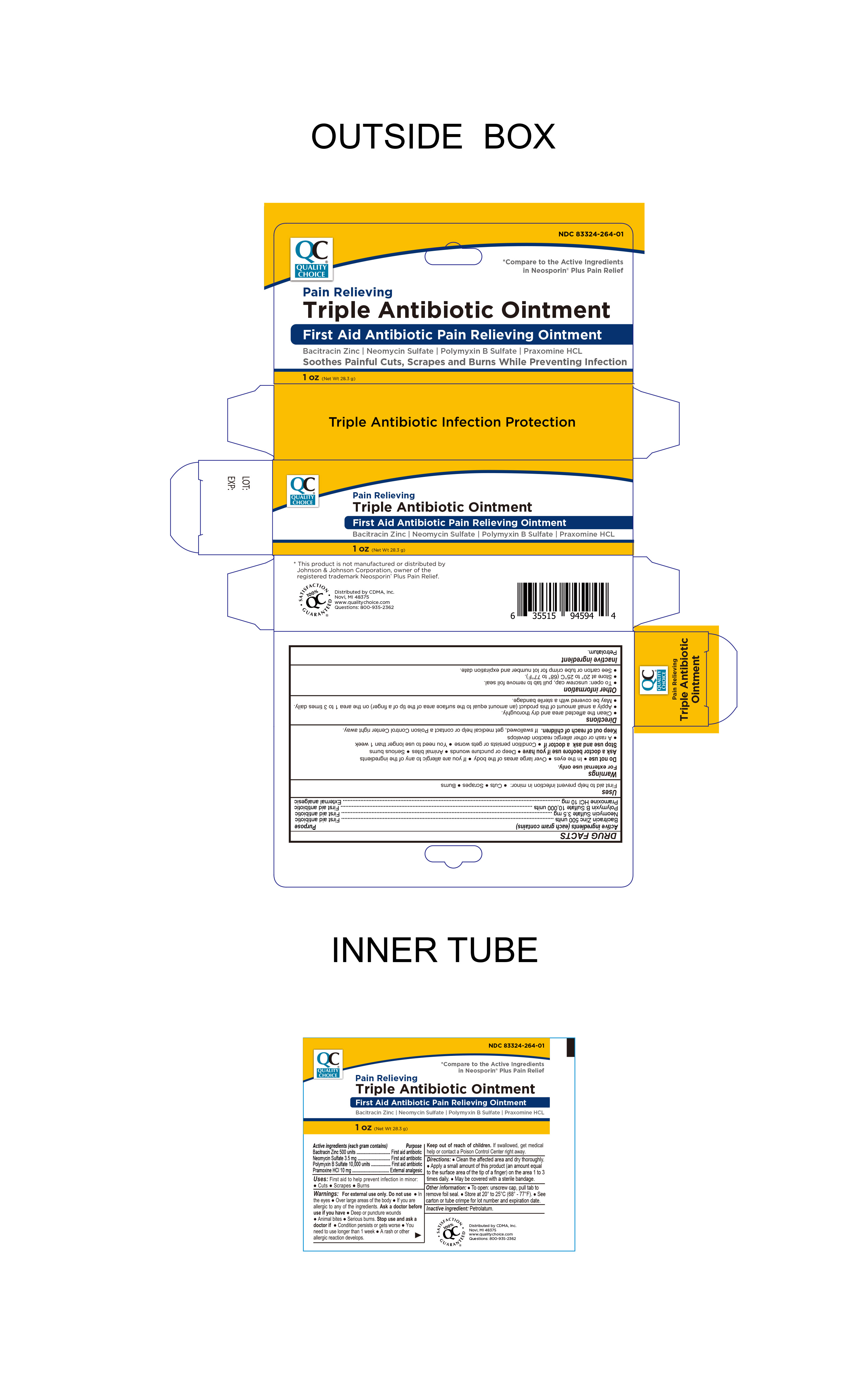 DRUG LABEL: Triple Antibiotic Plus Pain Relief
NDC: 83324-264 | Form: OINTMENT
Manufacturer: Chain Drug Marketing Association Inc.
Category: otc | Type: HUMAN OTC DRUG LABEL
Date: 20250826

ACTIVE INGREDIENTS: BACITRACIN ZINC 500 [USP'U]/1 g; NEOMYCIN SULFATE 3.5 mg/1 g; POLYMYXIN B SULFATE 10000 [USP'U]/1 g; PRAMOXINE HYDROCHLORIDE 10 mg/1 g
INACTIVE INGREDIENTS: PETROLATUM

Quality Choice Triple Antibiotic Ointment Plus Pain Relief

Active ingredients (each gram contains)

Bacitracin zinc 500 units
Neomycin sulfate 3.5 mg
Polymyxin B sulfate 10,000 units

Purpose

First aid antibiotic

Active Ingredient

Pramoxine HCL 10mg

Purpose

External Analgesic

Keep out of reach of children.If swallowed, get medical help or contact a Poison Control Center right away.

INDICATIONS AND USAGE

Uses first aid to help prevent infection in minor:● cuts ● scrapes ● burns

WARNINGS

WarningsFor external use only.

Do not use● in the eyes ● over large areas of the body

Ask a doctor before use if you have

● deep or puncture wounds ● animal bites ● serious burns.

Stop use and ask a doctor if● condition persists or gets worse

● you need to use longer than 1 week

● a rash or other allergic reaction develops

Directions

● clean the affected area and dry thoroughly.

● apply a small amount of this product (an amount equal to the surface area of the tip of a finger) on the area 1 to 3 times daily

● may be covered with a sterile bandage.

Inactive ingredient: Petrolatum

Other information

● To open: unscrew cap, pull tab to remove foil seal
● store at 20° to 25°C (68° to 77°F)

● see carton or tube crimp for lot number and expiration date.

Other Information

Distributed by C.D.M.A., Inc.

43157 W 9 Mile Rd

Novi, MI 48375

www.qualitychoice.com

questions: 800-935-2362

Product of PRC